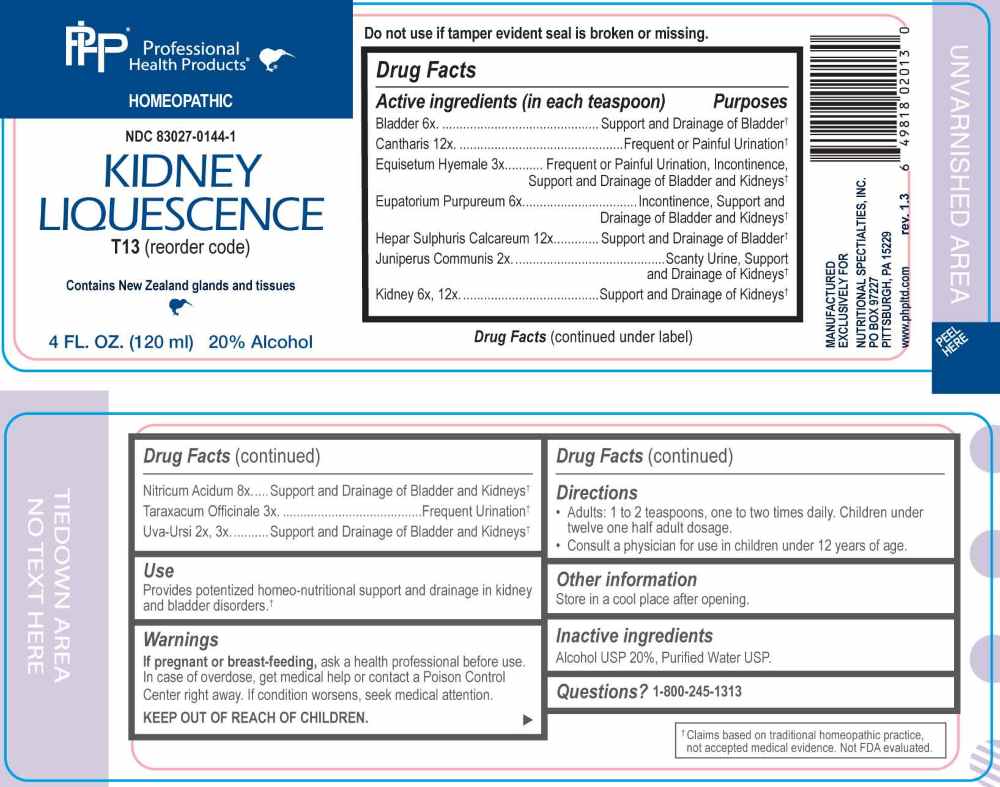 DRUG LABEL: Kidney Liquescence
NDC: 83027-0144 | Form: LIQUID
Manufacturer: Nutritional Specialties, Inc.
Category: homeopathic | Type: HUMAN OTC DRUG LABEL
Date: 20251008

ACTIVE INGREDIENTS: JUNIPER BERRY 2 [hp_X]/1 mL; ARCTOSTAPHYLOS UVA-URSI LEAF 2 [hp_X]/1 mL; EQUISETUM HYEMALE WHOLE 3 [hp_X]/1 mL; TARAXACUM OFFICINALE 3 [hp_X]/1 mL; SUS SCROFA URINARY BLADDER 6 [hp_X]/1 mL; EUTROCHIUM PURPUREUM ROOT 6 [hp_X]/1 mL; BEEF KIDNEY 6 [hp_X]/1 mL; NITRIC ACID 8 [hp_X]/1 mL; LYTTA VESICATORIA 12 [hp_X]/1 mL; CALCIUM SULFIDE 12 [hp_X]/1 mL
INACTIVE INGREDIENTS: WATER; alcohol

DRUG FACTS:

ACTIVE INGREDIENTS:

(in each teaspoon) Bladder 6X, Cantharis 12X, Equisetum Hyemale 3X, Eupatorium Purpureum 6X, Hepar Sulphuris Calcareum 12X, Juniperus Communis 2X, Kidney 6X, 12X, Nitricum Acidum 8X, Taraxacum Officinale 3X, Uva-Ursi 2X, 3X.

PURPOSE:

Bladder – Support and Drainage of Bladder,† Cantharis – Frequent or Painful Urination,† Equisetum Hyemale – Frequent or Painful Urination, Incontinence, Support and Drainage of Bladder and Kidneys,† Eupatorium Purpureum – Incontinence, Support and Drainage of Bladder and Kidneys,† Hepar Sulphuris Calcareum – Support and Drainage of Bladder,† Juniperus Communis – Scanty Urine, Support and Drainage of Kidneys,† Kidney – Support and Drainage of Kidneys,† Nitricum Acidum – Support and Drainage of Bladder and Kidneys,† Taraxacum Officinale – Frequent Urination,† Uva-Ursi – Support and Drainage of Bladder and Kidneys†

USES:

Provides potentized homeo-nutritional support and drainage in kidney and bladder disorders.†

†Claims based on traditional homeopathic practice, not accepted medical evidence. Not FDA evaluated.

WARNINGS:

If pregnant or breast-feeding, ask a health professional before use.

In case of overdose, get medical help or contact a Poison Control Center right away.

If condition worsens, seek medical attention.

KEEP OUT OF REACH OF CHILDREN

Do not use if tamper evident seal is broken or missing.

Store in a cool place after opening

KEEP OUT OF REACH OF CHILDREN:

In case of overdose, get medical help or contact a Poison Control Center right away.

DIRECTIONS:

• Adults: 1 to 2 teaspoons, one to two times daily. Children under twelve one half adult dosage.

• Consult a physician for use in children under 12 years of age.

INACTIVE INGREDIENTS:

Alcohol USP 20%, Purified Water USP.

QUESTIONS:

MANUFACTURED EXCLUSIVELY FOR

NUTRITIONAL SPECIALTIES, INC.

PO BOX 97227

PITTSBURG, PA 15229

www.phpltd.com

1-800-245-1313

PACKAGE LABEL DISPLAY:

Professional

Health Products

HOMEOPATHIC

NDC 83027-0144-1

KIDNEY LIQUESCENCE

4 FL. OZ (120 ml)